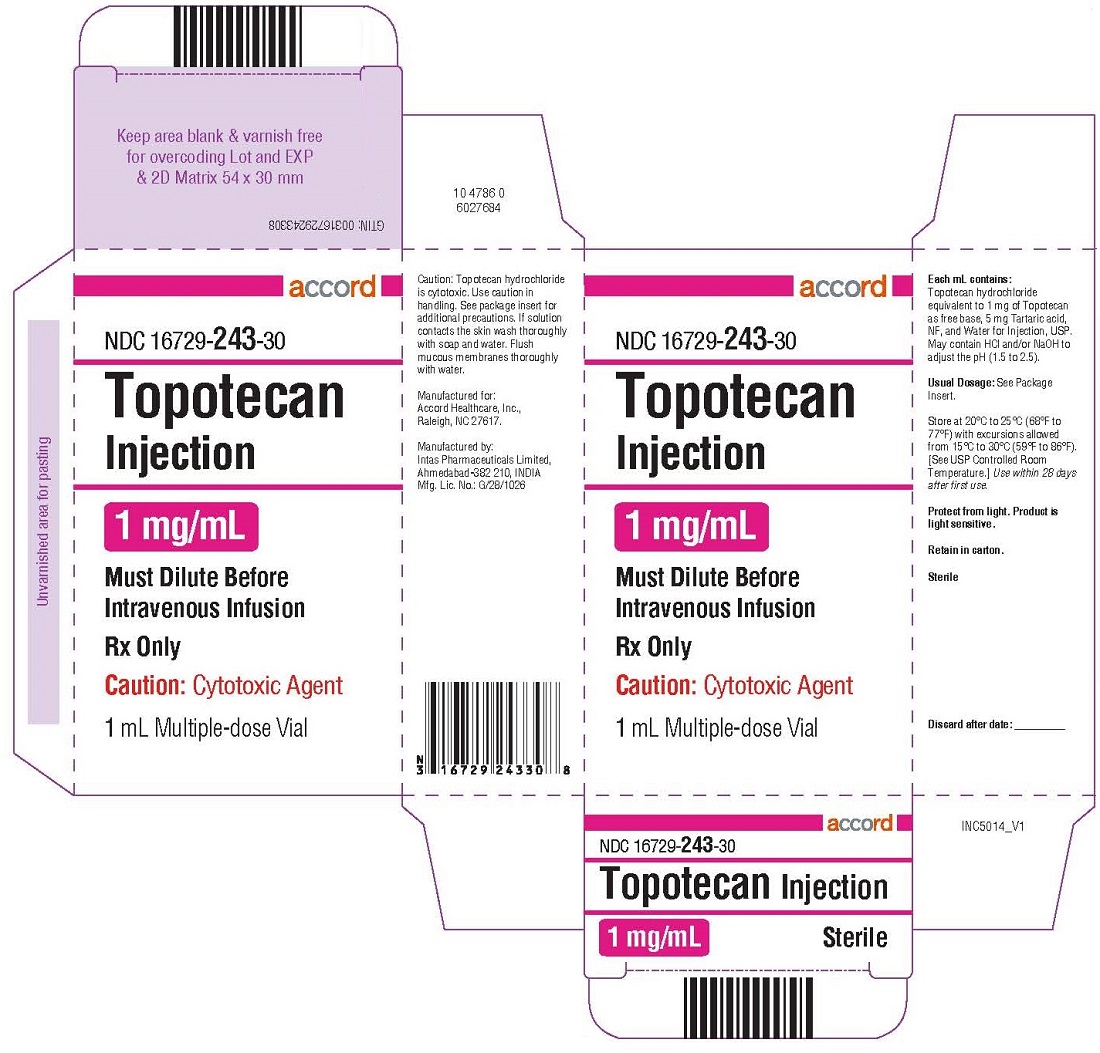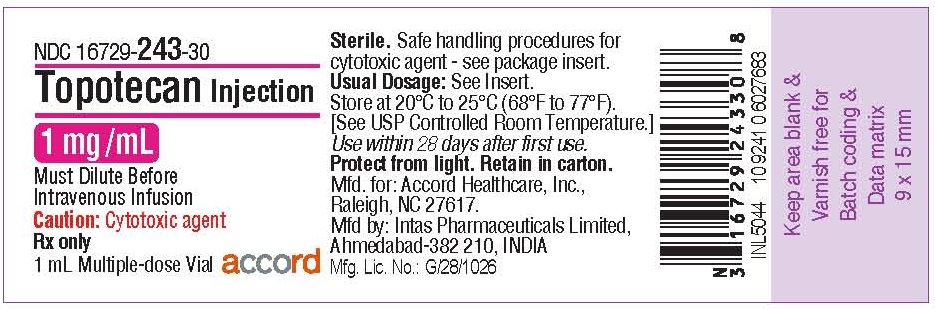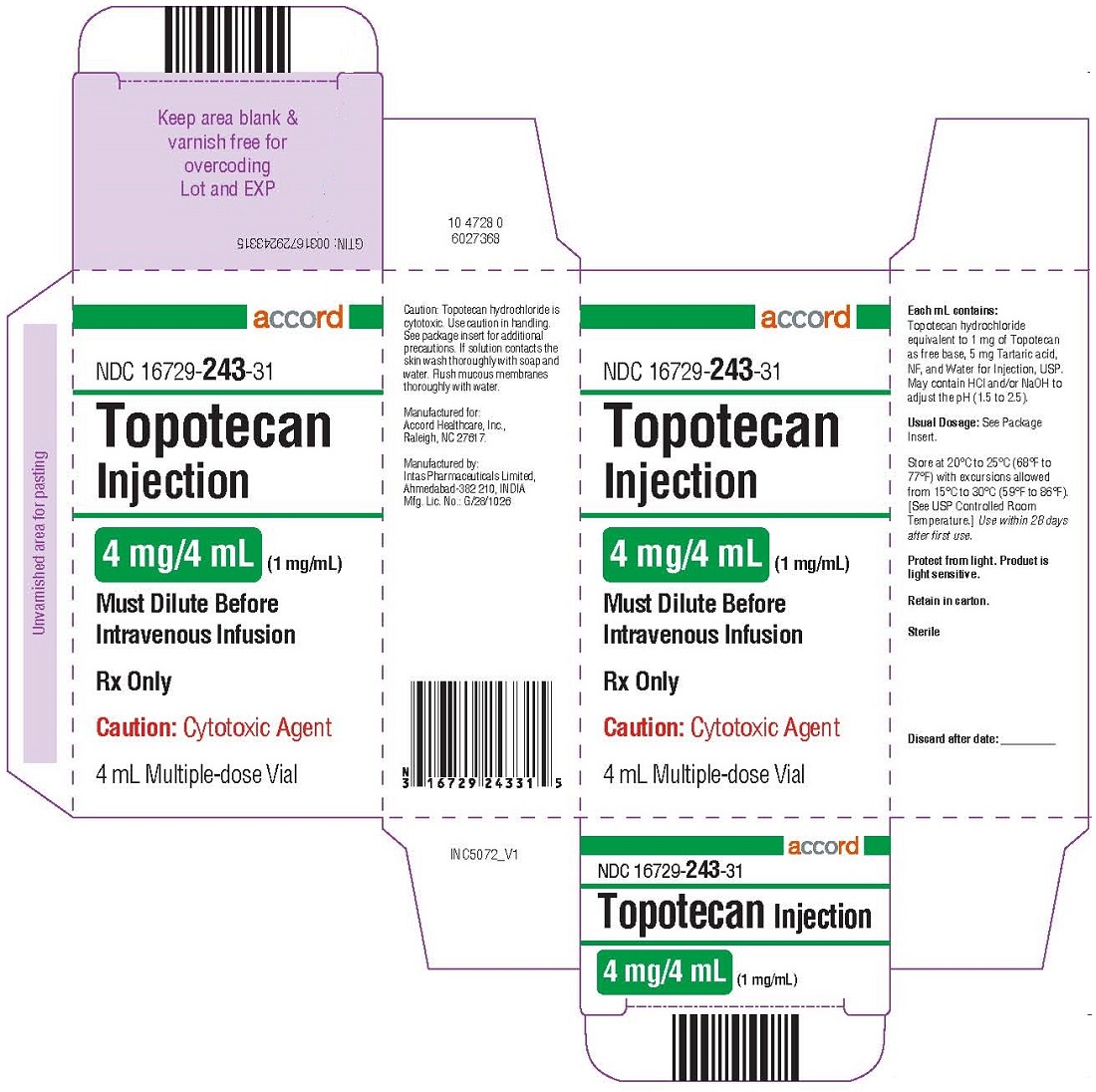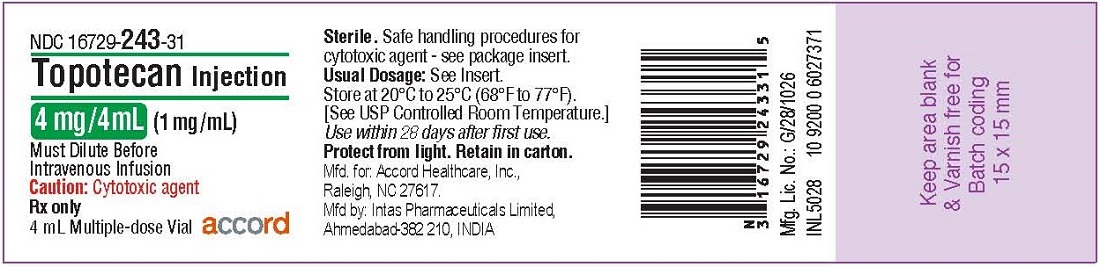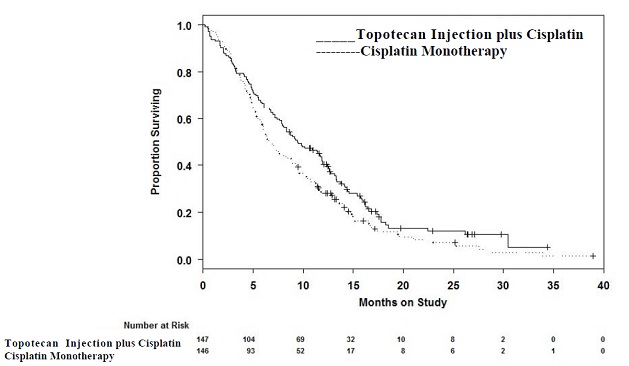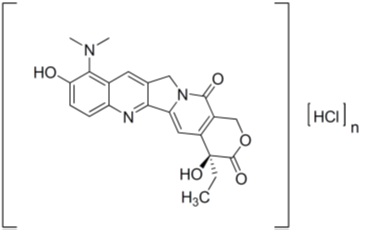 DRUG LABEL: Topotecan
NDC: 16729-243 | Form: INJECTION
Manufacturer: Accord Healthcare Inc.
Category: prescription | Type: HUMAN PRESCRIPTION DRUG LABEL
Date: 20251217

ACTIVE INGREDIENTS: TOPOTECAN 1 mg/1 mL
INACTIVE INGREDIENTS: WATER; TARTARIC ACID 5 mg/1 mL; HYDROCHLORIC ACID; SODIUM HYDROXIDE

HIGHLIGHTS OF PRESCRIBING INFORMATION

These highlights do not include all the information needed to use TOPOTECAN INJECTION safely and effectively.
See full prescribing information for TOPOTECAN INJECTION.
TOPOTECAN Injection
Must be diluted before intravenous infusion
Initial U.S. Approval: 1996

WARNING: BONE MARROW SUPPRESSION

See full prescribing information for complete boxed warning

Do not give Topotecan to patients with baseline neutrophil counts less than 1,500 cells/mm^3. In order to monitor the occurrence of bone marrow suppression, primarily neutropenia, which may be severe and result in infection and death, monitor peripheral blood cell counts frequently on all patients receiving Topotecan Injection. (5.1)

1 INDICATIONS AND USAGE

Topotecan is a topoisomerase inhibitor indicated for:

- small cell lung cancer sensitive disease after failure of first-line chemotherapy. (1)
- combination therapy with cisplatin for stage IV-B, recurrent, or persistent carcinoma of the cervix which is not amenable to curative treatment with surgery and/or radiation therapy. (1)

2 DOSAGE AND ADMINISTRATION

- Small cell lung cancer: 1.5 mg/m^2by intravenous infusion over 30 minutes daily for 5 consecutive days, starting on day one of a 21-day course. (2.1)
- Cervical cancer: 0.75 mg/m^2by intravenous infusion over 30 minutes on days 1, 2, and 3 followed by cisplatin 50 mg/m^2by intravenous infusion on day 1 repeated every 21 days. (2.2)

See Dosage Modification Guidelines for patients with neutropenia or reduced platelets.(2.1, 2.2)
See Dosage Adjustment in Renal Impairment. (2.3)

3 DOSAGE FORMS AND STRENGTHS

- 1 mg/mL Multiple Dose Vial
- 4 mg/4 mL (1 mg/mL) Multiple Dose Vial

Each mL contains topotecan hydrochloride equivalent to 1 mg of topotecan free base.

4 CONTRAINDICATIONS

- History of severe hypersensitivity reactions (e.g., anaphylactoid reactions) to topotecan or any of its ingredients (4)
- Severe bone marrow depression (4)

5 WARNINGS AND PRECAUTIONS

- Bone marrow suppression: Administer Topotecan Injection only to patients with adequate bone marrow reserves. Monitor peripheral blood counts and adjust the dose if needed. (5.1)
- Topotecan-induced neutropenia can lead to neutropenic colitis. (5.2)
- Interstitial lung disease: topotecan has been associated with reports of interstitial lung disease. Monitor patients for symptoms and discontinue Topotecan Injection if the diagnosis is confirmed. (5.3)
- Pregnancy: Can cause fetal harm. Advise women of potential risk to the fetus. (5.4, 8.1)

6 ADVERSE REACTIONS

Small cell lung cancer:

- The most common hematologic adverse reactions were: neutropenia (97%), leukopenia (97%), anemia (89%), and thrombocytopenia (69%). (6.1)
- The most common (>25%) non-hematologic adverse reactions (all grades) were: nausea, alopecia, vomiting, sepsis or pyrexia/infection with neutropenia, diarrhea, constipation, fatigue, and pyrexia. (6.1)

Cervical cancer (Topotecan Injection plus cisplatin):

- The most common hematologic adverse reactions (all grades) were: anemia (94%), leukopenia (91%), neutropenia (89%), and thrombocytopenia (74%). (6.1)
- The most common (>25%) non-hematologic adverse reactions (all grades) were: pain, nausea, vomiting, and infection/febrile neutropenia. (6.1)

To report SUSPECTED ADVERSE REACTIONS, contact Accord Healthcare Inc. at 1-866-941-7875or FDA at 1-800-FDA-1088 or www.fda.gov/medwatch

7 DRUG INTERACTIONS

- Do not initiate G-CSF until 24 hours after completion of treatment with Topotecan Injection. Concomitant administration can prolong duration of neutropenia. (7)
- Greater myelosuppression is likely to be seen when used in combination with other cytotoxic agents. (7)

8 USE IN SPECIFIC POPULATIONS

- Nursing Mothers: Discontinue nursing when receiving Topotecan Injection. (8.3)

FULL PRESCRIBING INFORMATION

WARNING: BONE MARROW SUPPRESSION

Do not give Topotecan Injection to patients with baseline neutrophil counts less than 1,500 cells/mm^3. In order to monitor the occurrence of bone marrow suppression, primarily neutropenia, which may be severe and result in infection and death, monitor peripheral blood counts frequently on all patients receiving Topotecan Injection. [see Warnings and Precautions (5.1) ]

1 INDICATIONS AND USAGE

Topotecan Injection is indicated for the treatment of:

- small cell lung cancer sensitive disease after failure of first-line chemotherapy. In clinical studies submitted to support approval, sensitive disease was defined as disease responding to chemotherapy but subsequently progressing at least 60 days (in the Phase 3 study) or at least 90 days (in the Phase 2 studies) after chemotherapy [see Clinical Studies (14) ] .

Topotecan Injection in combination with cisplatin is indicated for the treatment of:

- stage IV-B, recurrent, or persistent carcinoma of the cervix which is not amenable to curative treatment with surgery and/or radiation therapy.

2 DOSAGE AND ADMINISTRATION

Verify dose using body surface area prior to dispensing. Recommended dosage should not exceed 4 mg [see Overdosage 10].

Prior to administration of the first course of Topotecan Injection, patients must have a baseline neutrophil count of >1,500 cells/mm^3and a platelet count of >100,000 cells/mm^3.

2.1 Small Cell Lung Cancer

Recommended Dosage

- The recommended dose of topotecan is 1.5 mg/m^2by intravenous infusion over 30 minutes daily for 5 consecutive days, starting on day 1 of a 21-day course.
- In the absence of tumor progression, a minimum of 4 courses is recommended because tumor response may be delayed. The median time to response in 4 small cell lung cancer trials was 5 to 7 weeks.

Dosage Modification Guidelines

- In the event of severe neutropenia (defined as <500 cells/mm^3) during any course, reduce the dose by 0.25 mg/m^2(to 1.25 mg/m^2) for subsequent courses.
- Alternatively, in the event of severe neutropenia, administer G-CSF (granulocyte-colony stimulating factor) following the subsequent course (before resorting to dose reduction) starting from day 6 of the course (24 hours after completion of topotecan administration).
- In the event the platelet count falls below 25,000 cells/mm^3, reduce doses by 0.25 mg/m^2(to 1.25 mg/m^2) for subsequent courses.

2.2 Cervical Cancer

Recommended Dosage

The recommended dose of Topotecan Injection is 0.75 mg/m^2by intravenous infusion over 30 minutes daily on days 1, 2, and 3; followed by cisplatin 50 mg/m^2by intravenous infusion on day 1 repeated every 21 days (a 21-day course).

Dosage Modification Guidelines

Dosage adjustments for subsequent courses of Topotecan Injection in combination with cisplatin are specific for each drug. See manufacturer’s prescribing information for cisplatin administration and hydration guidelines and for cisplatin dosage adjustment in the event of hematologic toxicity

- In the event of severe febrile neutropenia (defined as <1000 cells/mm^3with temperature of 38°C or 100.4°F), reduce the dose of Topotecan Injection to 0.60 mg/m^2for subsequent courses.
- Alternatively, in the event of severe febrile neutropenia, administer G-CSF following the subsequent course (before resorting to dose reduction) starting from day 4 of the course (24 hours after completion of administration of Topotecan Injection).
- If febrile neutropenia occurs despite the use of G-CSF, reduce the dose of Topotecan Injection to 0.45 mg/m^2for subsequent courses.
- In the event the platelet count falls below 25,000 cells/mm^3, reduce doses to 0.60 mg/m^2for subsequent courses.

2.3 Dosage Adjustment in Specific Populations

Renal Impairment

No dosage adjustment of Topotecan Injection appears to be required for patients with mild renal impairment (Clcr40 to 60 mL/min.). Dosage adjustment of Topotecan Injection to 0.75 mg/m^2is recommended for patients with moderate renal impairment (20 to 39 mL/min.). Insufficient data are available in patients with severe renal impairment to provide a dosage recommendation for Topotecan Injection. [see Use in Specific Populations (8.6) and Clinical Pharmacology (12.3) ]

Topotecan Injection in combination with cisplatin for the treatment of cervical cancer should only be initiated in patients with serum creatinine ≤1.5 mg/dL. In the clinical trial, cisplatin was discontinued for a serum creatinine >1.5 mg/dL. Insufficient data are available regarding continuing monotherapy with Topotecan Injection after cisplatin discontinuation in patients with cervical cancer.

2.4 Instructions for Handling, Preparation and Intravenous Administration

Handling

Topotecan is a cytotoxic anticancer drug. Prepare Topotecan Injection under a vertical laminar flow hood while wearing gloves and protective clothing. If Topotecan Injection solution contacts the skin, wash the skin immediately and thoroughly with soap and water. If Topotecan Injection contacts mucous membranes, flush thoroughly with water.

Use procedures for proper handling and disposal of anticancer drugs. Several guidelines on this subject have been published.^1-4

Preparation and Administration

The appropriate volume of the Topotecan Injection is diluted in a minimum of 50 mL of 0.9% Sodium Chloride Injection, USP or 5% Dextrose Injection, USP prior to administration. Infuse over 30 minutes. Topotecan Injection diluted for infusion is stable for 4 hours at room temperature or 24 hours at refrigerated temperature in ambient lighting conditions.

Topotecan Injection is supplied as a multiple dose vial. Studies have shown the product is stable for 28 days after initial puncture when stored at room temperature.

3 DOSAGE FORMS AND STRENGTHS

Topotecan Injection is available in the following strengths:

1 mg/mL Multiple Dose Vial

4 mg/4 mL (1 mg/mL) Multiple Dose Vial

Each mL contains topotecan hydrochloride equivalent to 1 mg of topotecan free base for intravenous infusion only following dilution.

4 CONTRAINDICATIONS

Topotecan Injection is contraindicated in patients who have a history of severe hypersensitivity reactions (e.g., anaphylactoid reactions) to topotecan or to any of its ingredients. Topotecan Injection should not be used in patients with severe bone marrow depression.

5 WARNINGS AND PRECAUTIONS

5.1 Bone Marrow Suppression

Bone marrow suppression (primarily neutropenia) is the dose-limiting toxicity of Topotecan Injection. Neutropenia is not cumulative over time. In the comparative study, in small cell lung cancer, the treatment-related death rates were 5% for topotecan and 4% for CAV (cyclophosphamide-doxorubicin-vincristine).

Neutropenia

- From a combined experience of patients receiving topotecan which included patients treated for small cell lung cancer: Grade 4 neutropenia (<500 cells/mm^3) was most common during course 1 of treatment (60% of patients) and occurred in 39% of all courses, with a median duration of 7 days. The nadir neutrophil count occurred at a median of 12 days. Therapy-related sepsis or febrile neutropenia occurred in 23% of patients, and sepsis was fatal in 1%. Pancytopenia has been reported.
- Cervical cancer experience: Grade 3 and grade 4 neutropenia affected 26 % and 48 % of patients, respectively.

Thrombocytopenia

- From a combined experience of patients receiving topotecan which included patients treated for small cell lung cancer: Grade 4 thrombocytopenia (<25,000/mm^3) occurred in 27% of patients and in 9% of courses, with a median duration of 5 days and platelet nadir at a median of 15 days. Platelet transfusions were given to 15% of patients in 4% of courses.
- Cervical cancer experience: Grade 3 and grade 4 thrombocytopenia affected 26 % and 7 % of patients, respectively.

Anemia

- From a combined experience of patients receiving topotecan which included patients treated for small cell lung cancer: Grade 3/4 anemia (<8 g/dL) occurred in 37% of patients and in 14% of courses. Median nadir was at day 15. Transfusions were needed in 52% of patients in 22% of courses.
- Cervical cancer experience: Grade 3 and grade 4 anemia affected 34 % and 6 % of patients, respectively.

Monitoring of Bone Marrow Function

Administer Topotecan Injection only in patients with adequate bone marrow reserves, including baseline neutrophil count of at least 1,500 cells/mm^3and platelet count at least 100,000/mm^3.

Monitor peripheral blood counts frequently during treatment with Topotecan Injection. Do not treat patients with subsequent courses of Topotecan Injection until neutrophils recover to >1,000 cells/mm^3, platelets recover to >100,000 cells/mm^3, and hemoglobin levels recover to 9 g/dL (with transfusion if necessary).Severe myelotoxicity has been reported when Topotecan Injection is used in combination with cisplatin [see Drug Interactions (7) ]

5.2 Neutropenic Colitis

Topotecan-induced neutropenia can lead to neutropenic colitis. Fatalities due to neutropenic colitis have been reported in clinical trials with Topotecan Injection. In patients presenting with fever, neutropenia, and a compatible pattern of abdominal pain, consider the possibility of neutropenic colitis.

5.3 Interstitial Lung Disease

Topotecan Injection has been associated with reports of interstitial lung disease (ILD), some of which have been fatal [see Adverse Reactions (6.2) ]. Underlying risk factors include history of ILD, pulmonary fibrosis, lung cancer, thoracic exposure to radiation, and use of pneumotoxic drugs and/or colony stimulating factors. Monitor patients for pulmonary symptoms indicative of interstitial lung disease (e.g., cough, fever, dyspnea, and/or hypoxia), and discontinue Topotecan Injection if a new diagnosis of ILD is confirmed.

5.4 Pregnancy

Pregnancy Category D

Topotecan Injection can cause fetal harm when administered to a pregnant woman.

Topotecan caused embryolethality, fetotoxicity, and teratogenicity in rats and rabbits when administered during organogenesis. There are no adequate and well controlled studies of Topotecan Injection in pregnant women. If this drug is used during pregnancy, or if a patient becomes pregnant while receiving Topotecan Injection, the patient should be apprised of the potential hazard to the fetus. [see Use in Specific Populations, Pregnancy (8.1) ]

5.5 Inadvertent Extravasation

Inadvertent extravasation with topotecan has been observed, most reactions have been mild but severe cases have been reported.

6 ADVERSE REACTIONS

6.1 Clinical Trials Experience

Because clinical trials are conducted under widely varying conditions, adverse reaction rates observed in the clinical trials of a drug cannot be directly compared to rates in the clinical trials of another drug and may not reflect the rates observed in practice.

Small Cell Lung Cancer

Data in the following section are based on the combined experiences of the 879 patients studied, including 426 patients with small cell lung cancer treated with topotecan. Table 1lists the principle hematologic adverse reactions and Table 2lists non-hematologic adverse reactions occurring in at least 15% of patients.

Table 1. Hematologic Adverse Reactions Experienced in ≥15% of Patients, Including 426 Patients With Small Cell Lung Cancer, Receiving Topotecan
Hematologic Adverse Reaction | Patients; (n=879); % Incidence
Neutropenia; <1,500 cells/mm^3; <500 cells/mm^3 | 97; 78
Leukopenia; <3,000 cells/mm^3; <1,000 cells/mm^3 | 97; 32
Thrombocytopenia; <75,000/mm^3; <25,000/mm^3 | 69; 27
Anemia; <10 g/dL; <8 g/dL | 89; 37

Table 2. Non-hematologic Adverse Reactions Experienced by ≥15% of 879 Patients, Including 426 Patients With Small Cell Lung Cancer, Receiving Topotecan
Non-hematologic; Adverse Reaction | Percentage of Patients with Adverse Reaction (879 Patients)
Non-hematologic; Adverse Reaction | All Grades | Grade 3 | Grade 4
Non-hematologic; Adverse Reaction
Infections and infestations
Sepsis or pyrexia/infection with neutropeniaa | 43 | NR | 23
Metabolism and nutrition disorders
Anorexia | 19 | 2 | <1
Nervous system disorders
Headache | 18 | 1 | <1
Respiratory, thoracic, and mediastinal disorders
Dyspnea | 22 | 5 | 3
Coughing | 15 | 1 | 0
Gastrointestinal disorders
Nausea | 64 | 7 | 1
Vomiting | 45 | 4 | 1
Diarrhea | 32 | 3 | 1
Constipation | 29 | 2 | 1
Abdominal pain | 22 | 2 | 2
Stomatitis | 18 | 1 | <1
Skin and subcutaneous tissue disorders
Alopecia | 49 | NA | NA
Rashb | 16 | 1 | 0
General disorders and administrative site conditions
Fatigue | 29 | 5 | 0
Pyrexia | 28 | 1 | <1
Painc | 23 | 2 | 1
Asthenia | 25 | 4 | 2

NA = Not applicable

NR = Not reported separately

aDoes not include Grade 1 sepsis or pyrexia

bRash also includes pruritus, rash erythematous, urticaria, dermatitis, bullous eruption, and maculopapular rash.

cPain includes body pain, back pain, and skeletal pain.

Nervous System Disorders

Paresthesia occurred in 7% of patients but was generally grade 1.

Hepatobiliary Disorders

Grade 1 transient elevations in hepatic enzymes occurred in 8% of patients. Greater elevations, grade 3/4, occurred in 4%. Grade 3/4 elevated bilirubin occurred in <2% of patients.

Table 3shows the grade 3/4 hematologic and major non-hematologic adverse reactions in the topotecan/CAV comparator trial in small cell lung cancer.

Table 3. Adverse Reactions Experienced by ≥5% of Small Cell Lung Cancer Patients Randomized to Receive Topotecan or CAV

Adverse Reaction | Topotecan; (n=107) | CAV; (n=104)
Hematologic Grade 3/4 | % | %
Grade 4 neutropenia; (<500 cells/mm^3) | 70 | 72
Grade 3/4 anemia; (Hgb <8 g dL) | 42 | 20
Grade 4 thrombocytopenia; (<25,000 plts/mm^3) | 29 | 5
Pyrexia/Grade 4 neutropenia | 28 | 26
Non-hematologic Grade 3/4 | % | %
Infections and infestations; Documented sepsisa | 5 | 5
Respiratory, thoracic, and mediastinal disorders; Dyspnea | 9 | 14
Pneumonia | 8 | 6
Gastrointestinal disorders; Abdominal pain | 6 | 4
Nausea | 8 | 6
General disorders and administrative site conditions; Fatigue | 6 | 10
Asthenia | 9 | 7
Painb | 5 | 7

aDeath related to sepsis occurred in 3% of patients receiving topotecan, and in 1% of patients receiving CAV

bPain includes body pain, skeletal pain, and back pain.

Cervical Cancer

In the comparative trial with Topotecan Injection plus cisplatin versus cisplatin in patients with cervical cancer, the most common dose-limiting adverse reaction was myelosuppression. Table 4shows the hematologic adverse reactions and Table 5shows the non-hematologic adverse reactions in patients with cervical cancer.

Table 4. Hematologic Adverse Reactions in Patients with Cervical Cancer Treated with Topotecan Injection Plus Cisplatin or Cisplatin Monotherapya
Hematologic Adverse Reaction | Topotecan Injection Plus Cisplatin; (n = 140) | Cisplatin; (n = 144)
Anemia
All grades (Hgb <12 g/dL) | 131 (94%) | 130 (90%)
Grade 3 (Hgb <8 to 6.5 g/dL) | 47 (34%) | 28 (19%)
Grade 4 (Hgb <6.5 g/dL) | 9 (6%) | 5 (3%)
Leukopenia
All grades (<3,800 cells/mm^3) | 128 (91%) | 43 (30%)
Grade 3 (<2,000 to 1,000 cells/mm^3) | 58 (41%) | 1 (1%)
Grade 4 (<1,000 cells/mm^3) | 35 (25%) | 0 (0%)
Neutropenia
All grades (<2,000 cells/mm^3) | 125 (89%) | 28 (19%)
Grade 3 (<1,000 to 500 cells/mm^3) | 36 (26%) | 1 (1%)
Grade 4 (<500 cells/mm^3) | 67 (48%) | 1 (1%)
Thrombocytopenia
All grades (<130,000 cells/mm^3) | 104 (74%) | 21 (15%)
Grade 3 (<50,000 to 10,000 cells/mm^3) | 36 (26%) | 5 (3%)
Grade 4 (<10,000 cells/mm^3) | 10 (7%) | 0 (0%)

aIncludes patients who were eligible and treated.

Table 5. Non-hematologic Adverse Reactions Experienced by ≥ 5% of Patients with Cervical Cancer Treated with Topotecan Injection Plus Cisplatin or Cisplatin Monotherapya
 | Topotecan Injection Plus Cisplatin |  |  | Cisplatin
 | (n = 140) |  |  | (n = 144)
Adverse Reaction | All Gradesb | Grade 3 | Grade 4 | All Gradesb | Grade 3 | Grade 4
General disorders and administrative site conditions
Constitutionalc | 96 (69%) | 11 (8%) | 0 | 89 (62%) | 17 (12%) | 0
Paind | 82 (59%) | 28 (20%) | 3 (2%) | 72 (50%) | 18 (13%) | 5 (3%)
Gastrointestinal disorders
Vomiting | 56 (40%) | 20 (14%) | 2 (1%) | 53 (37%) | 13 (9%) | 0
Nausea | 77 (55%) | 18 (13%) | 2 (1%) | 79 (55%) | 13 (9%) | 0
Stomatitis-pharyngitis | 8 (6%) | 1 (<1%) | 0 | 0 | 0 | 0
Other | 88 (63%) | 16 (11%) | 4 (3%) | 80 (56%) | 12 (8%) | 3 (2%)
Dermatology | 67 (48%) | 1 (<1%) | 0 | 29 (20%) | 0 | 0
Metabolic-Laboratory | 55 (39%) | 13 (9%) | 7 (5%) | 44 (31%) | 14 (10%) | 1 (<1%)
Genitourinary | 51 (36%) | 9 (6%) | 9 (6%) | 49 (34%) | 7 (5%) | 7 (5%)
Nervous system disorders
Neuropathy | 4 (3%) | 1 (<1%) | 0 | 3 (2%) | 1 (<1%) | 0
Other | 49 (35%) | 3 (2%) | 1 (<1%) | 43 (30%) | 7 (5%) | 2 (1%)
Infection-febrile neutropenia | 39 (28%) | 21 (15%) | 5 (4%) | 26 (18%) | 11 (8%) | 0
Cardiovascular | 35 (25%) | 7 (5%) | 6 (4%) | 22 (15%) | 8 (6%) | 3 (2%)
Hepatic | 34 (24%) | 5 (4%) | 2 (1%) | 23 (16%) | 2 (1%) | 0
Pulmonary | 24 (17%) | 4 (3%) | 0 | 23 (16%) | 5 (3%) | 3 (2%)
Vascular disorders
Hemorrhage | 21 (15%) | 8 (6%) | 1 (<1%) | 20 (14%) | 3 (2%) | 1 (<1%)
Coagulation | 8 (6%) | 4 (3%) | 3 (2%) | 10 (7%) | 7 (5%) | 0
Musculoskeletal | 19 (14%) | 3 (2%) | 0 | 7 (5%) | 1 (<1%) | 1 (<1%)
Allergy-Immunology | 8 (6%) | 2 (1%) | 1 (<1%) | 4 (3%) | 0 | 1 (<1%)
Endocrine | 8 (6%) | 0 | 0 | 4 (3%) | 2 (1%) | 0
Sexual reproduction function | 7 (5%) | 0 | 0 | 10 (7%) | 1 (<1%) | 0
Ocular-visual | 7 (5%) | 0 | 0 | 7 (5%) | 1 (<1%) | 0

Data were collected using NCI Common Toxicity Criteria, v. 2.0.

aIncludes patients who were eligible and treated.

bGrades 1 through 4 only. There were 3 patients who experienced grade 5 deaths with investigator-designated attribution. One was a grade 5 hemorrhage in which the drug-related thrombocytopenia aggravated the event. A second patient experienced bowel obstruction, cardiac arrest, pleural effusion and respiratory failure which were not treatment related but probably aggravated by treatment. A third patient experienced a pulmonary embolism and adult respiratory distress syndrome, the latter was indirectly treatment-related.

cConstitutional includes fatigue (lethargy, malaise, asthenia), fever (in the absence of neutropenia), rigors, chills, sweating, and weight gain or loss.

dPain includes abdominal pain or cramping, arthralgia, bone pain, chest pain (non-cardiac and non-pleuritic), dysmenorrhea, dyspareunia, earache, headache, hepatic pain, myalgia, neuropathic pain, pain due to radiation, pelvic pain, pleuritic pain, rectal or perirectal pain, and tumor pain.

6.2 Postmarketing Experience

In addition to adverse reactions reported from clinical trials or listed in other sections of the prescribing information, the following reactions have been identified during post-marketing use of Topotecan Injection. Because they are reported voluntarily from a population of unknown size, estimates of frequency cannot be made. These reactions have been chosen for inclusion due to a combination of their seriousness, frequency of reporting, or potential causal connection to Topotecan Injection.

Blood and Lymphatic System Disorders:Severe bleeding (in association with thrombocytopenia). [see Warnings and Precautions (5.1) ]

Immune System Disorders:Allergic manifestations; Anaphylactoid reactions.

Gastrointestinal Disorders:Abdominal pain potentially associated with neutropenic colitis. [see Warnings and Precautions (5.2) ]

Pulmonary Disorders:Interstitial lung disease [see Warnings and Precautions (5.3) ]

Skin and Subcutaneous Tissue Disorders:Angioedema, severe dermatitis, severe pruritus

General Disorders and Administration Site Conditions:Inadvertent extravasation [see Warnings and Precautions (5.5) ]

7 DRUG INTERACTIONS

G-CSF:Concomitant administration of G-CSF can prolong the duration of neutropenia, so if G-CSF is to be used, do not initiate it until day 6 of the course of therapy, 24 hours after completion of treatment with Topotecan Injection.

Platinum and Other Cytotoxic Agents:Myelosuppression was more severe when topotecan, at a dose of 1.25 mg/m^2/day for 5 days, was given in combination with cisplatin at a dose of 50 mg/m^2in Phase 1 studies. In one study, 1 of 3 patients had severe neutropenia for 12 days and a second patient died with neutropenic sepsis.

Greater myelosuppression is also likely to be seen when Topotecan Injection is used in combination with other cytotoxic agents, thereby necessitating a dose reduction. However, when combining topotecan with platinum agents (e.g., cisplatin or carboplatin), a distinct sequence-dependent interaction on myelosuppression has been reported. Coadministration of a platinum agent on day 1 of dosing with topotecan required lower doses of each agent compared to co-administration on day 5 of the dosing schedule for topotecan.

For information on the pharmacokinetics, efficacy, safety, and dosing of Topotecan Injection at a dose of 0.75 mg/m^2/day on days 1, 2, and 3 in combination with cisplatin 50 mg/m^2on day 1 for cervical cancer [see Dosage and Administration (2) , Adverse Reactions (6), Clinical Pharmacology (12.3) and Clinical Studies (14) ] .

8 USE IN SPECIFIC POPULATIONS

8.1 Pregnancy

Pregnancy Category D [see Warnings and Precautions (5.4) ].

Topotecan Injection can cause fetal harm when administered to a pregnant woman. In rabbits, a dose of 0.1 mg/kg/day (about equal to the clinical dose of 1.5 mg/m^2) given on days 6 through 20 of gestation caused maternal toxicity, embryolethality, and reduced fetal body weight. In the rat, a dose of 0.23 mg/kg/day (about equal to the clinical dose of 1.5 mg/m^2) given for 14 days before mating through gestation day 6 caused fetal resorption, microphthalmia, pre-implant loss, and mild maternal toxicity. A dose of 0.1 mg/kg/day (about half the clinical dose of 1.5 mg/m^2) given to rats on days 6 through 17 of gestation caused an increase in post-implantation mortality. This dose also caused an increase in total fetal malformations. The most frequent malformations were of the eye (microphthalmia, anophthalmia, rosette formation of the retina, coloboma of the retina, ectopic orbit), brain (dilated lateral and third ventricles), skull, and vertebrae.

There are no adequate and well controlled studies of Topotecan Injection in pregnant women. If this drug is used during pregnancy, or if a patient becomes pregnant while receiving Topotecan Injection, the patient should be apprised of the potential hazard to the fetus. [see Warnings and Precautions (5.4) ]

8.3 Nursing Mothers

Rats excrete high concentrations of topotecan into milk. Lactating female rats given 4.72 mg/m^2IV (about three times the clinical dose of 1.5 mg/m^2) excreted topotecan into milk at concentrations up to 48-fold higher than those in plasma. It is not known whether the drug is excreted in human milk. Because many drugs are excreted in human milk and because of the potential for serious adverse reactions in nursing infants from Topotecan Injection, discontinue breastfeeding when women are receiving Topotecan Injection.

8.4 Pediatric Use

Safety and effectiveness in pediatric patients have not been established.

8.5 Geriatric Use

Of the 879 patients in a combined experience of topotecan which included patients with small cell lung cancer, 32% (n=281) were 65 years of age and older, while 3.8% (n=33) were 75 years of age and older. Of the 140 patients with stage IV-B, relapsed, or refractory cervical cancer in clinical studies of Topotecan Injection who received Topotecan Injection plus cisplatin in the randomized clinical trial, 6% (n = 9) were 65 years of age and older, while 3% (n = 4) were 75 years of age and older.

No overall differences in effectiveness or safety were observed between these patients and younger adult patients, and other reported clinical experience has not identified differences in responses between the elderly and younger adult patients, but greater sensitivity of some older individuals cannot be ruled out.

There were no apparent differences in the pharmacokinetics of topotecan in elderly patients, once the age-related decrease in renal function was considered [see Clinical Pharmacology (12.3) ].

This drug is known to be substantially excreted by the kidney, and the risk of toxic reactions to this drug may be greater in patients with impaired renal function. Because elderly patients are more likely to have decreased renal function, care should be taken in dose selection, and it may be useful to monitor renal function [see Dosage and Administration (2.3) ].

8.6 Renal Impairment

No dosage adjustment of Topotecan Injection appears to be required for patients with mild renal impairment (Clcr40 to 60 mL/min.). Dosage reduction is recommended for patients with moderate renal impairment (Clcr20 to 39 mL/min.). Insufficient data are available in patients with severe renal impairment to provide a dosage recommendation for Topotecan Injection. [see Dosage and Administration (2.3) and Clinical Pharmacology (12.3) ].

10 OVERDOSAGE

Overdoses (up to 10-fold of the prescribed dose) occurred in patients treated with intravenous topotecan. The primary complication of overdosage is bone marrow suppression. The observed signs and symptoms of overdose are consistent with the known adverse reactions associated with Topotecan Injection for intravenous use [see Adverse Reactions (6.1, 6.2) ]. In addition, elevated hepatic enzymes and mucositis have been reported following overdose.

One patient received a single dose of 40 mg/m^2of intravenous topotecan and developed gastrointestinal toxicity, skin toxicity, and myelosuppression leading to septic shock. Another patient received a single dose of 35 mg/m^2and experienced severe, reversible neutropenia.

There is no known antidote for overdosage with Topotecan Injection. If an overdose is suspected, monitor the patient for bone marrow suppression and institute supportive-care measures (such as prophylactic G-CSF and antibiotic therapy) as appropriate.

11 DESCRIPTION

Topotecan is a semi-synthetic derivative of camptothecin and is an anti-tumor drug with topoisomerase I-inhibitory activity.

The chemical name for topotecan free base is (S)-10-[(dimethylamino)methyl]-4-ethyl-4,9-dihydroxy-1 H-pyrano[3’,4’:6,7]indolizino[1,2- b]quinoline-3,14-(4 H,12 H)-dione. It has the molecular formula C23H23N3O5and a molecular weight of 421.45.

Topotecan has three pKa values: pKa1= 10.50 corresponding to the benzyldimethylamino group, pKa2= 6.99 corresponding to the phenol group and pKa3= 0.60 corresponding to the quinoline group.

As formulated in Topotecan Injection, topotecan has the following structural formula:

where n is >1, corresponding to HCl added to adjust the pH to approximately 1.5 to 2.5.

Topotecan Injection is supplied as a sterile, non-pyrogenic, clear, yellow solution at a topotecan free base concentration of 4 mg/4 mL (1 mg/mL) and 1 mg/mL available in multiple dose vials. Each mL of Topotecan Injection contains topotecan hydrochloride equivalent to 1 mg of topotecan as free base, 5 mg tartaric acid, NF, and water for injection, USP. Hydrochloric acid and/or sodium hydroxide may be used to adjust the pH.. The hydrochloride salt of topotecan is soluble in water and melts with decomposition at 213°C to 218°C.

The solution must be diluted before administration by intravenous infusion.

12 CLINICAL PHARMACOLOGY

12.1 Mechanism of Action

Topoisomerase I relieves torsional strain in DNA by inducing reversible single strand breaks. Topotecan binds to the topoisomerase I-DNA complex and prevents religation of these single strand breaks. The cytotoxicity of topotecan is thought to be due to double strand DNA damage produced during DNA synthesis, when replication enzymes interact with the ternary complex formed by topotecan, topoisomerase I, and DNA. Mammalian cells cannot efficiently repair these double strand breaks.

12.2 Pharmacodynamics

The dose-limiting toxicity of topotecan is leukopenia. White blood cell count decreases with increasing topotecan dose or topotecan AUC. When topotecan is administered at a dose of 1.5 mg/m^2/day for 5 days, an 80% to 90% decrease in white blood cell count at nadir is typically observed after the first cycle of therapy.

12.3 Pharmacokinetics

The pharmacokinetics of topotecan have been evaluated in cancer patients following doses of 0.5 to 1.5 mg/m^2administered as a 30-minute infusion. Topotecan exhibits multiexponential pharmacokinetics with a terminal half-life of 2 to 3 hours. Total exposure (AUC) is approximately dose-proportional.

Distribution:Binding of topotecan to plasma proteins is about 35%.

Metabolism:Topotecan undergoes a reversible pH dependent hydrolysis of its lactone moiety; it is the lactone form that is pharmacologically active. At pH ≤ 4, the lactone is exclusively present, whereas the ring-opened hydroxy-acid form predominates at physiologic pH. In vitrostudies in human liver microsomes indicate topotecan is metabolized to an N-demethylated metabolite. The mean metabolite:parent AUC ratio was about 3% for total topotecan and topotecan lactone following IV administration.

Excretion:Renal clearance is an important determinant of topotecan elimination.

In a mass balance/excretion study in 4 patients with solid tumors, the overall recovery of total topotecan and its N-desmethyl metabolite in urine and feces over 9 days averaged 73.4 ± 2.3% of the administered IV dose. Mean values of 50.8 ± 2.9% as total topotecan and 3.1 ± 1.0% as N-desmethyl topotecan were excreted in the urine following IV administration. Fecal elimination of total topotecan accounted for 17.9 ± 3.6% while fecal elimination of N-desmethyl topotecan was 1.7 ± 0.6%. An O-glucuronidation metabolite of topotecan and N-desmethyl topotecan has been identified in the urine. These metabolites, topotecan-O-glucuronide and N-desmethyl topotecan-O-glucuronide, were less than 2% of the administered dose.

Effect of Gender:The overall mean topotecan plasma clearance in male patients was approximately 24% higher than that in female patients, largely reflecting difference in body size.

Effect of Age:Topotecan pharmacokinetics have not been specifically studied in an elderly population, but population pharmacokinetic analysis in female patients did not identify age as a significant factor. Decreased renal clearance, which is common in the elderly, is a more important determinant of topotecan clearance [see Dosage and Administration (2.3) and Use in Specific Populations (8.5) ].

Effect of Race:The effect of race on topotecan pharmacokinetics has not been studied.

Effect of Renal Impairment:In patients with mild renal impairment (creatinine clearance of 40 to 60 mL/min.), topotecan plasma clearance was decreased to about 67% of the value in patients with normal renal function. In patients with moderate renal impairment (Clcrof 20 to 39 mL/min.), topotecan plasma clearance was reduced to about 34% of the value in control patients, with an increase in half-life. Mean half-life, estimated in 3 renally impaired patients, was about 5.0 hours. Dosage adjustment is recommended for these patients [see Dosage and Administration (2.3) ].

Effect of Hepatic Impairment:Plasma clearance in patients with hepatic impairment (serum bilirubin levels between 1.7 and 15.0 mg/dL) was decreased to about 67% of the value in patients without hepatic impairment. Topotecan half-life increased slightly, from 2.0 hours to 2.5 hours, but these hepatically impaired patients tolerated the usual recommended topotecan dosage regimen.

Drug Interactions:Pharmacokinetic studies of the interaction of topotecan with concomitantly administered medications have not been formally investigated.

In vitroinhibition studies using marker substrates known to be metabolized by human P450 CYP1A2, CYP2A6, CYP2C8/9, CYP2C19, CYP2D6, CYP2E, CYP3A, or CYP4A or dihydropyrimidine dehydrogenase indicate that the activities of these enzymes were not altered by topotecan. Enzyme inhibition by topotecan has not been evaluated in vivo.

Cisplatin:No pharmacokinetic data are available following topotecan (0.75 mg/m^2/day for 3 consecutive days) and cisplatin (50 mg/m^2/day on day 1) in patients with cervical cancer. Myelosuppression was more severe when topotecan was given in combination with cisplatin. [see Drug Interactions(7)].

13 NONCLINICAL TOXICOLOGY

13.1 Carcinogenesis, Mutagenesis, Impairment of Fertility

Carcinogenicity testing of topotecan has not been performed. Topotecan is known to be genotoxic to mammalian cells and is a probable carcinogen. Topotecan was mutagenic to L5178Y mouse lymphoma cells and clastogenic to cultured human lymphocytes with and without metabolic activation. It was also clastogenic to mouse bone marrow. Topotecan did not cause mutations in bacterial cells.

Topotecan given to female rats prior to mating at a dose of 1.4 mg/m^2IV (about equal to the clinical dose of 1.5 mg/m^2) caused superovulation possibly related to inhibition of follicular atresia. This dose given to pregnant female rats also caused increased pre-implantation loss. Studies in dogs given 0.4 mg/m^2IV (about 1/4th the clinical dose of 1.5 mg/m^2) of topotecan daily for a month suggest that treatment may cause an increase in the incidence of multinucleated spermatogonial giant cells in the testes. Topotecan may impair fertility in women and men.

14 CLINICAL STUDIES

14.1 Small Cell Lung Cancer

Topotecan was studied in 426 patients with recurrent or progressive small cell lung cancer in 1 randomized, comparative study and in 3 single-arm studies.

Randomized Comparative Study

In a randomized, comparative, Phase 3 trial, 107 patients were treated with topotecan (1.5 mg/m^2/day x 5 days starting on day 1 of a 21-day course) and 104 patients were treated with CAV (1,000 mg/m^2cyclophosphamide, 45 mg/m^2doxorubicin, 2 mg vincristine administered sequentially on day 1 of a 21-day course). All patients were considered sensitive to first-line chemotherapy (responders who then subsequently progressed ≥60 days after completion of first-line therapy). A total of 77% of patients treated with topotecan and 79% of patients treated with CAV received platinum/etoposide with or without other agents as first-line chemotherapy.

Response rates, response duration, time to progression, and survival are shown in Table 6.

Table 6. Efficacy of Topotecan Versus CAV (cyclophosphamide-doxorubicin-vincristine) in Small Cell Lung Cancer Patients Sensitive to First-Line Chemotherapy
Parameter | Topotecan; (n = 107) | CAV; (n = 104)
Complete response rate Partial response rate Overall response rate | 0% 24% 24% | 1% 17% 18%
Difference in overall response rates 95% Confidence interval of the difference | 6% (–6 to 18%)
Response durationa(weeks) Median 95% Confidence interval Hazard-ratio | n = 26 14.4 13.1 to 18 | n = 19 15.3 13.1 to 23.1
(Topotecan:CAV) (95% CI) (P-value) | 1.42 (0.73 to 2.76) (0.30)
Time to progression (weeks) Median 95% Confidence interval Hazard ratio | 13.3 11.4 to 16.4 | 12.3 11 to 14.1
(Topotecan:CAV) (95% CI) (P-value) | 0.92 (0.69 to 1.22) (0.55)
Survival (weeks) Median 95% Confidence interval Hazard ratio | 25 20.6 to 29.6 | 24.7 21.7 to 30.3
(Topotecan:CAV) (95% CI) (P-value) | 1.04 (0.78 to 1.39) (0.8)

aThe calculation for duration of response was based on the interval between first response and time to progression.

The time to response was similar to both arms: topotecan median of 6 weeks (range 2.4 to 15.7) versus CAV median 6 weeks (range 5.1 to 18.1).

Changes on a disease-related symptom scale in patients who received topotecan or who received CAV are presented in Table 7. It should be noted that not all patients had all symptoms, nor did all patients respond to all questions. Each symptom was rated on a 4-category scale with an improvement defined as a change in 1 category from baseline sustained over 2 courses. Limitations in interpretation of the rating scale and responses preclude formal statistical analysis.

Table 7. Percentage of Patients with Symptom Improvementa: Topotecan Versus CAV in Patients with Small Cell Lung Cancer
Symptom | Topotecan Injection; (n=107) |  | CAV; (n=104)
Symptom | nb | (%) | nb | (%)
Shortness of breath | 68 | (28) | 61 | (7)
Interference with daily activity | 67 | (27) | 63 | (11)
Fatigue | 70 | (23) | 65 | (9)
Hoarseness | 40 | (33) | 38 | (13)
Cough | 69 | (25) | 61 | (15)
Insomnia | 57 | (33) | 53 | (19)
Anorexia | 56 | (32) | 57 | (16)
Chest pain | 44 | (25) | 41 | (17)
Hemoptysis | 15 | (27) | 12 | (33)

aDefined as improvement sustained over at least 2 courses compared to baseline.

bNumber of patients with baseline and at least 1 post-baseline assessment.

Single-Arm Studies

Topotecan was also studied in 3 open-label, non-comparative trials in a total of 319 patients with recurrent or progressive small cell lung cancer after treatment with first-line chemotherapy. In all 3 studies, patients were stratified as either sensitive (responders who then subsequently progressed ≥90 days after completion of first-line therapy) or refractory (no response to first-line chemotherapy or who responded to first-line therapy and then progressed within 90 days of completing first-line therapy). Response rates ranged from 11% to 31% for sensitive patients and 2% to 7% for refractory patients. Median time to progression and median survival were similar in all 3 studies and the comparative study.

14.2 Cervical Cancer

In a comparative trial, 147 eligible women were randomized to Topotecan Injection (0.75 mg/m^2/day IV over 30 minutes × 3 consecutive days starting on day 1 of a 21-day course) plus cisplatin (50 mg/m^2on day 1) and 146 eligible women were randomized to cisplatin (50 mg/m^2IV on day 1 of a 21-day course). All patients had histologically confirmed Stage IV-B, recurrent, or persistent carcinoma of the cervix considered not amenable to curative treatment with surgery and/or radiation. Fifty-six percent (56%) of patients treated with Topotecan Injection plus cisplatin and 56% of patients treated with cisplatin had received prior cisplatin with or without other agents as first-line chemotherapy.

Median survival of eligible patients receiving Topotecan Injection plus cisplatin was 9.4 months (95% CI: 7.9 to 11.9) compared to 6.5 months (95% CI: 5.8 to 8.8) among patients randomized to cisplatin alone with a log rank P-value of 0.033 (significance level was 0.044 after adjusting for the interim analysis). The unadjusted hazard ratio for overall survival was 0.76 (95% CI: 0.59 to 0.98).

Figure 1. Overall Survival Curves Comparing Topotecan Injection plus Cisplatin versus Cisplatin Monotherapy in Cervical Cancer Patients

15 REFERENCES

1. Preventing Occupational Exposures to Antineoplastic and Other Hazardous Drugs in Health Care Settings. NIOSH Alert 2004-165.

2.OSHA Technical Manual, TED 1-0.15A, Section VI: Chapter 2. Controlling Occupational Exposure to Hazardous Drugs. OSHA, 1999. http://www.osha.gov/ dts/osta/otm/otm_vi/otm_vi_2.html

3. American Society of Health-System Pharmacists. ASHP Guidelines on Handling Hazardous Drugs. Am J Health-Syst Pharm. 2006;63:1172-1193.

4. Polovich M, White JM, Kelleher LO (eds.) 2005. Chemotherapy and Biotherapy Guidelines and Recommendations for Practice. (2nded) Pittsburgh, PA: Oncology Nursing Society.

16 HOW SUPPLIED/STORAGE AND HANDLING

Topotecan Injection is supplied in the following:

1 mg/mL Multiple Dose Vial

NDC 16729-243-30 (package of 1)

4 mg/4 mL (1 mg/mL) Multiple Dose Vial

NDC 16729-243-31 (package of 1)

Unopened vials of Topotecan Injection are stable until the date indicated on the package when stored at controlled room temperature between 20ºC and 25°C (68°F and 77°F) with excursions allowed from 15°C to 30°C (59°F to 86°F). Retain in carton to protect from light.

Topotecan Injection is supplied as a multiple dose vial. Studies have shown the product is stable for 28 days after initial puncture when stored at room temperature.

Topotecan Injection diluted for infusion is stable for 4 hours at room temperature or 24 hours at refrigerated temperature in ambient lighting conditions.

17 PATIENT COUNSELING INFORMATION

17.1 Bone Marrow Suppression

Inform patients that Topotecan Injection decreases blood cell counts such as white blood cells, platelets, and red blood cells. Patients who develop fever, other signs of infection (e.g., chills, cough, or burning pain on urination), or bleeding while on therapy should notify their physician promptly. Inform patients that frequent blood tests will be performed while taking Topotecan Injection to monitor for the occurrence of bone marrow suppression.

17.2 Pregnancy and Breastfeeding

Advise patients to use effective contraceptive measures to prevent pregnancy and to avoid breastfeeding during treatment with Topotecan Injection.

17.3 Asthenia and Fatigue

Inform patients that Topotecan Injection may cause asthenia or fatigue. If these symptoms occur, caution should be observed when driving or operating machinery.

Rx only

Manufactured for:
Accord Healthcare, Inc.,
8041 Arco Corporate Drive,
Suite 200,
Raleigh, NC 27617,
USA.

Manufactured by:
Intas Pharmaceuticals Limited,
Plot No.: 457, 458, Village – Matoda,
Bavla Road, Ta.- Sanand,
Dist.- Ahmedabad – 382 210,
INDIA.

10 7121 0 6027367

Issued December 2023

Principal Display Panel - 1 mg/mL Container Label

Principal Display Panel - 1 mg/mL Carton

Principal Display Panel - 4 mg/4 mL Container Label

Principal Display Panel - 4 mg/4 mL Carton